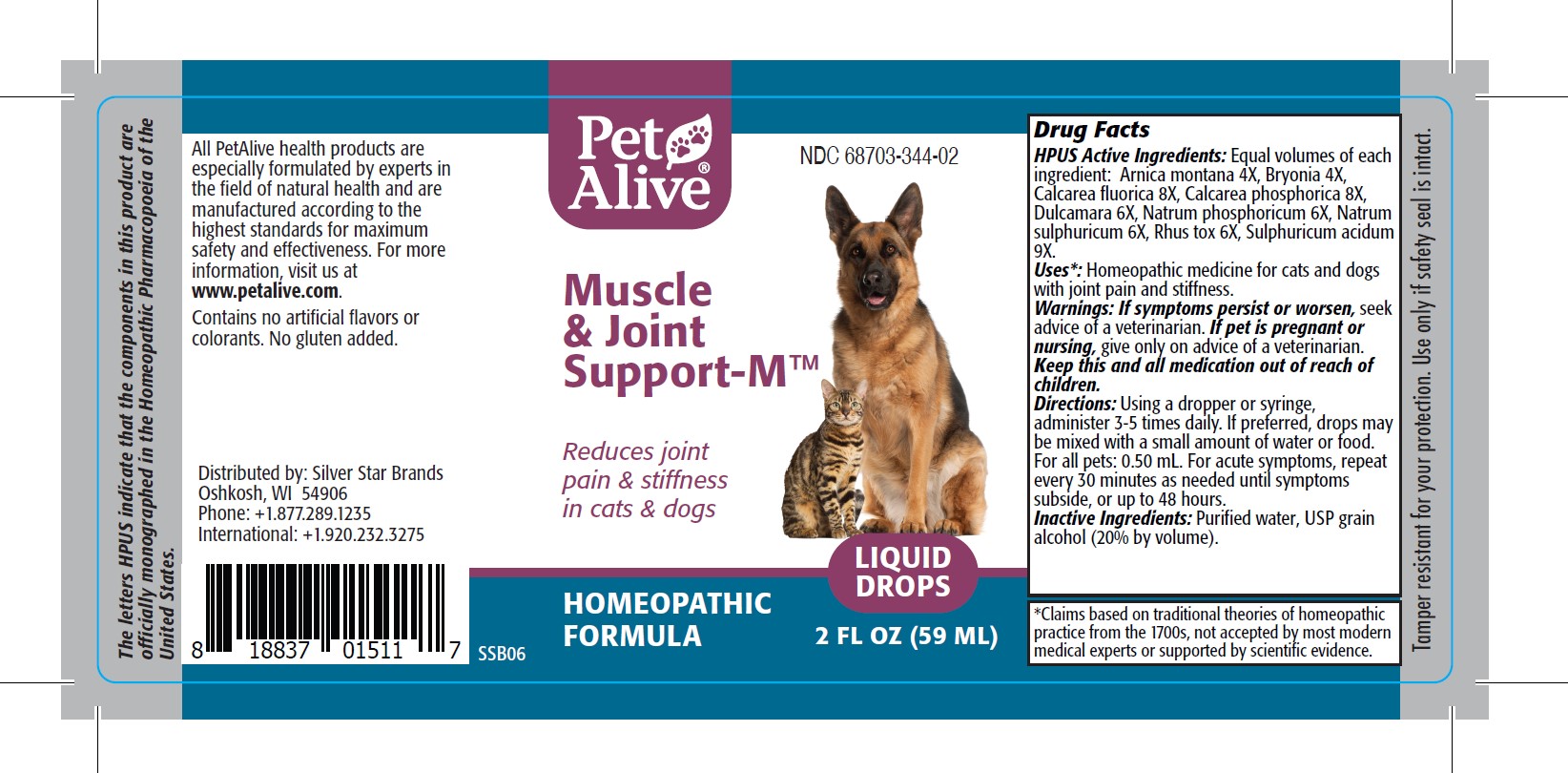 DRUG LABEL: Pet Alive Muscle and Joint Support-M
NDC: 68703-344 | Form: TINCTURE
Manufacturer: SILVER STAR BRANDS
Category: homeopathic | Type: OTC ANIMAL DRUG LABEL
Date: 20251216

ACTIVE INGREDIENTS: ARNICA MONTANA 4 [hp_X]/1 mL; BRYONIA ALBA ROOT 4 [hp_X]/1 mL; CALCIUM FLUORIDE			 8 [hp_X]/1 mL; TRIBASIC CALCIUM PHOSPHATE 8 [hp_X]/1 mL; SOLANUM DULCAMARA TOP 6 [hp_X]/1 mL; SODIUM PHOSPHATE, DIBASIC, HEPTAHYDRATE 6 [hp_X]/1 mL; SODIUM SULFATE 6 [hp_X]/1 mL; TOXICODENDRON PUBESCENS LEAF  6 [hp_X]/1 mL; SULFURIC ACID 9 [hp_X]/1 mL
INACTIVE INGREDIENTS: ALCOHOL; WATER

PetAlive Muscle and Joint Support-M

PURPOSE

Reduces joint pain and stiffness in cats and dogs

HPUS Active Ingredients:

Arnica montana 4X
Bryonia 4X
Calcarea fluorica 8X
Calcarea phosphorica 8X
Dulcamara 6X
Natrum phosphoricum 6X
Natrum sulphuricum 6X
Rhus tox 6X
Sulphuricum acidum 9X

INDICATIONS AND USAGE

Uses: Homeopathic medicine for cats and dogs with joint pain and stiffness

WARNINGS

Warnings: If symptoms persist or worsen, seek advice of a veterinarian

PREGNANCY OR BREAST FEEDING

If pet is pregnant or nursing, give only on advice of a veterinarian

KEEP OUT OF REACH OF CHILDREN

Keep this and all medication out of reach of children

DOSAGE AND ADMINISTRATION

Directions: Using a dropper or syringe, administer 3-5 times daily. If preferred, drops may be mixed with a small amount of water or food. For all pets: 0.50 mL. For acute symptoms, repeat every 30 minutes as needed until symptoms subside, or up to 48 hours.

INACTIVE INGREDIENT

Inactive Ingredients: Purified water, USP grain alcohol (20% by volume).

INFORMATION FOR OWNERS/CAREGIVERS

The letters HPUS indicate that the components in this product are officially monographed in the Homeopathic Pharmacopoeia of the United States.

All PetAlive health products are especially formulated by experts in the field of natural health and are manufactured according to the highest standards for maximum safety and effectiveness. For more information, visit us at www.petalive.com.

Contains no artificial flavors or colorants. No gluten added.

Distributed by: Silver Star Brands
Oshkosh, WI 54906
Phone: +1.877.289.1235
International: +1.920.232.3275

STORAGE AND HANDLING

Tamper resistant for your protection. Use only if safety seal is intact